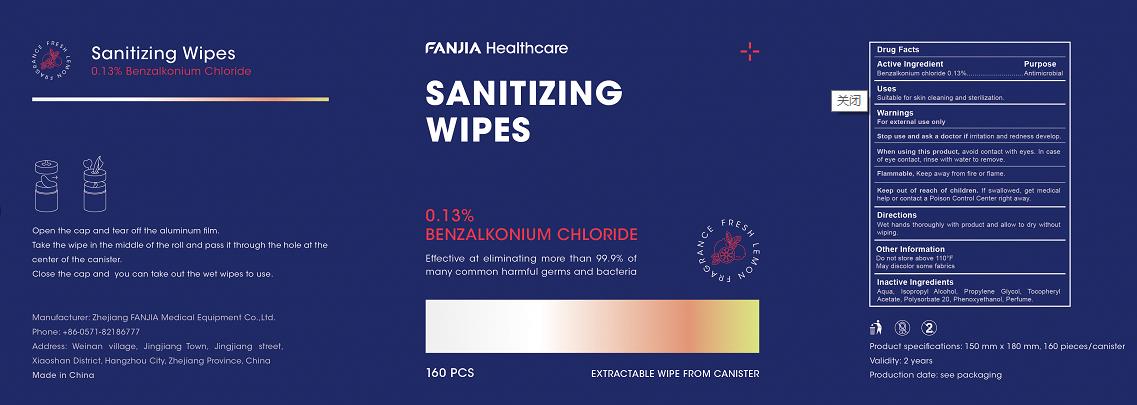 DRUG LABEL: Sanitizing Wipes
NDC: 80991-003 | Form: CLOTH
Manufacturer: Zhejiang Fanjia Medical Equipment Co., Ltd.
Category: otc | Type: HUMAN OTC DRUG LABEL
Date: 20210106

ACTIVE INGREDIENTS: BENZALKONIUM CHLORIDE 0.13 g/100 g
INACTIVE INGREDIENTS: POLYSORBATE 20; PHENOXYETHANOL; PROPYLENE GLYCOL; ISOPROPYL ALCOHOL; .ALPHA.-TOCOPHEROL ACETATE, D-; WATER; FAGRAEA BERTEROANA FLOWER OIL

0.13ben fanjia

Active Ingredient(s)

benzalkonium chloride 0.13%

Purpose

Antimicrobial

Inactive ingredients

Aqua,Isopropyl alcohol, Propylene glycol, Tocopherol acetate, polysorbote 20, phenoxyethanol, Perfume

Uses

Suitable for skin cleaning and sterilization

Warnings

For external use only.

Flammable,keep away from fire or flame

Do not use

- on open skin wounds

When using this product, avoid contact with eyes.In case of contact with eyes, rinse with water to remove.

Stop use and ask a doctor if irritation or redness develop.

Keep out of reach of children. If swallowed, get medical help or contact a Poison Control Center right away

Directions

- Wet hands thoroughly with product and allow to dry without wiping

Other information

- Do not store above 110F
- May discolor some fabrics

Package Label - Principal Display Panel

160PCS NDC 80991-003-04